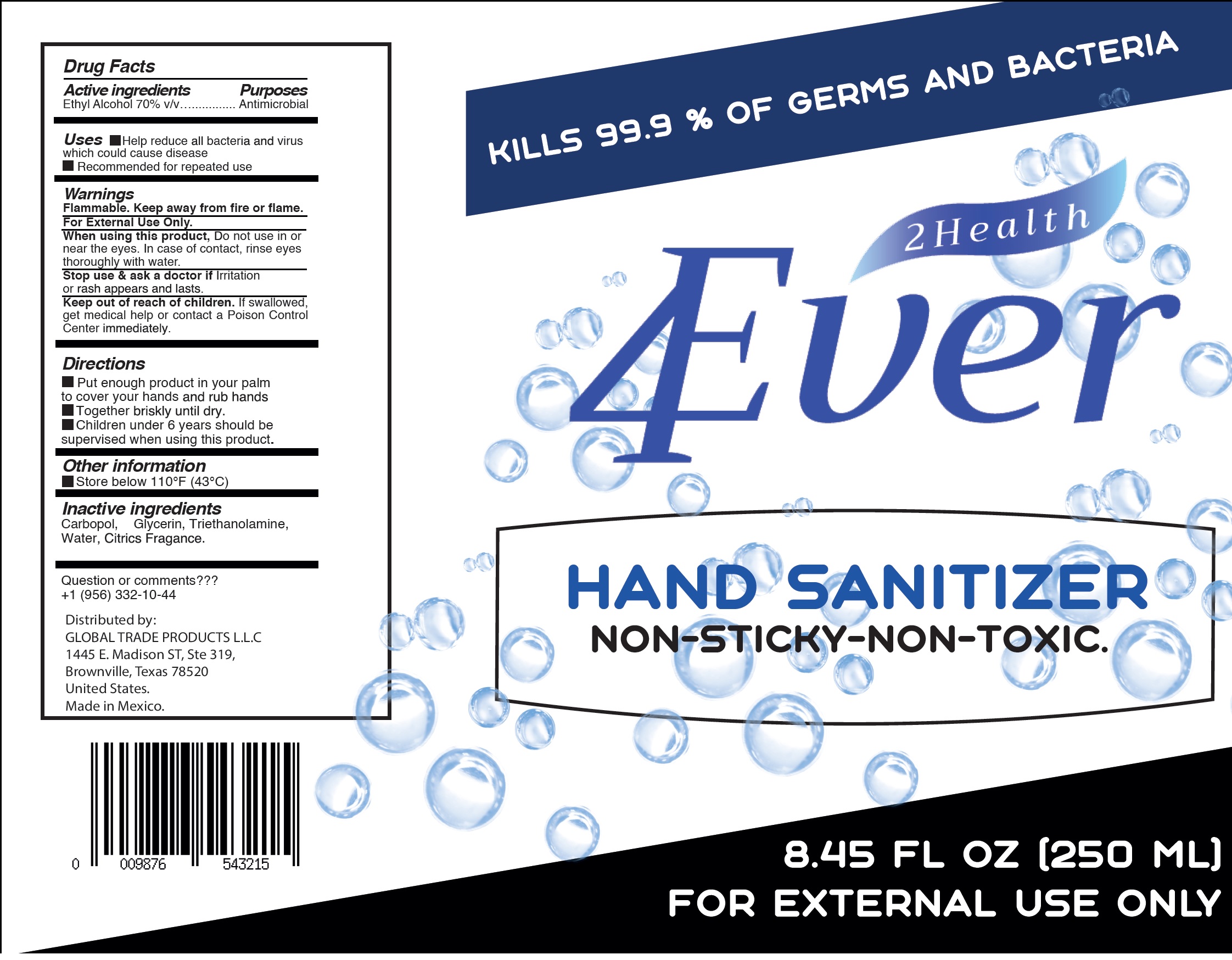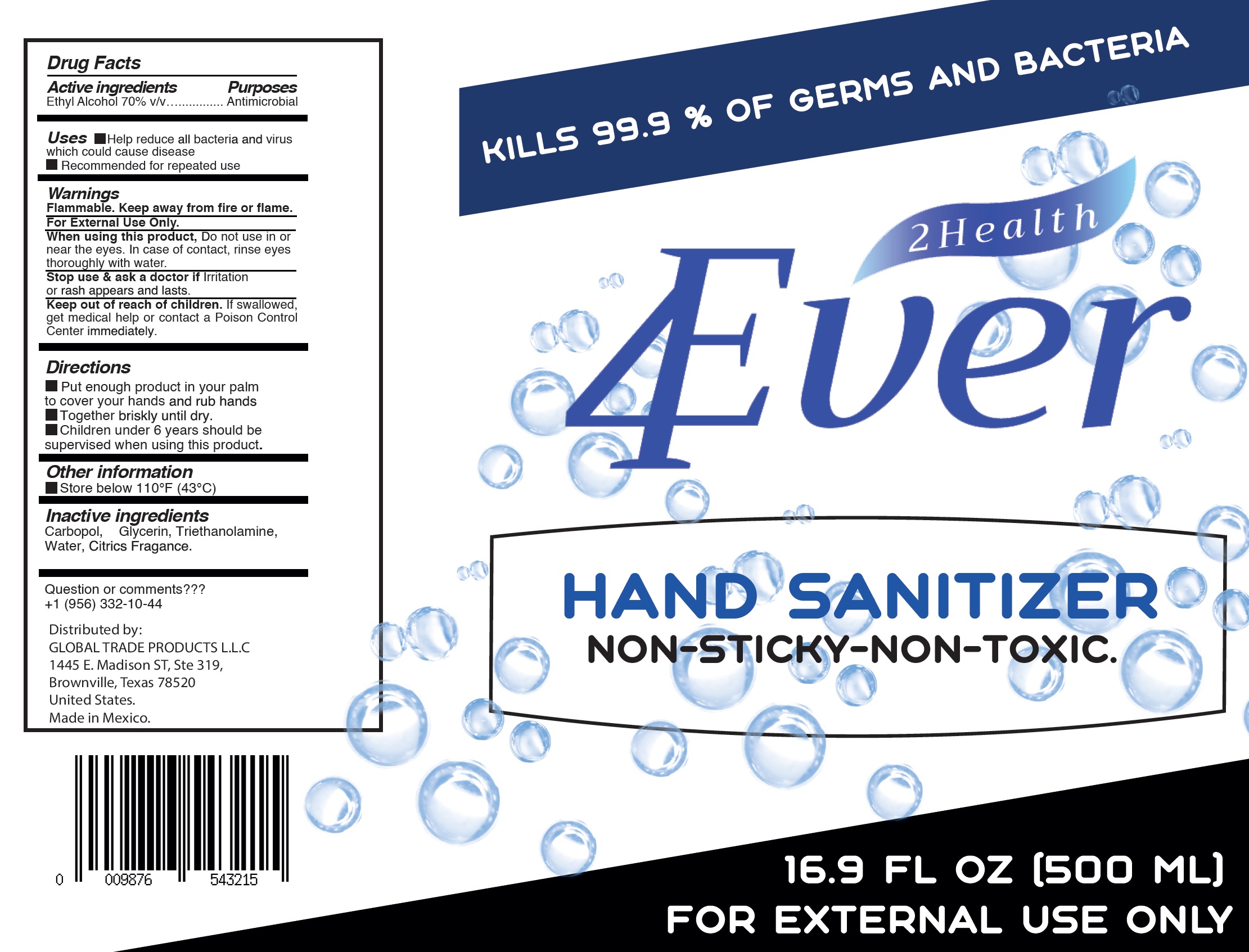 DRUG LABEL: 2Health 4ever Hand Sanitizer
NDC: 80916-000 | Form: GEL
Manufacturer: Jp Inter Trade, S.A. de C.V.
Category: otc | Type: HUMAN OTC DRUG LABEL
Date: 20201102

ACTIVE INGREDIENTS: ALCOHOL 0.7 mL/1 mL
INACTIVE INGREDIENTS: CARBOMER HOMOPOLYMER, UNSPECIFIED TYPE; GLYCERIN; TROLAMINE; WATER

2Health 4ever Hand Sanitizer

Active ingredients

Ethyl Alcohol 70% v/v

Purposes

Antimicrobial

Uses

- Help reduce bacteria and virus which could cause disease
- Recommended for repeated use

Warnings

Flammable. Keep away from fire or flame.
For External Use Only.

When using this product,

Do not use in or near the eyes. In case of contact, rinse eyes thoroughly with water.

Stop use & ask a doctor if

Irritation or rash appears and lasts.

Keep out of reach of children.

If swallowed, get medical help or contact a Poison Control Center immediately.

Directions

- Put enough product in your palm to cover your hands and rub hands
- Together briskly until dry.
- Children under 6 years should be supervised when using this product.

Other information

- Store below 110°F (43°C)

Inactive ingredients

Carbopol, Glycerin, Triethanolamine, Water, Citrics Fragrance.

Question or comments???

+1 (956) 332-10-44